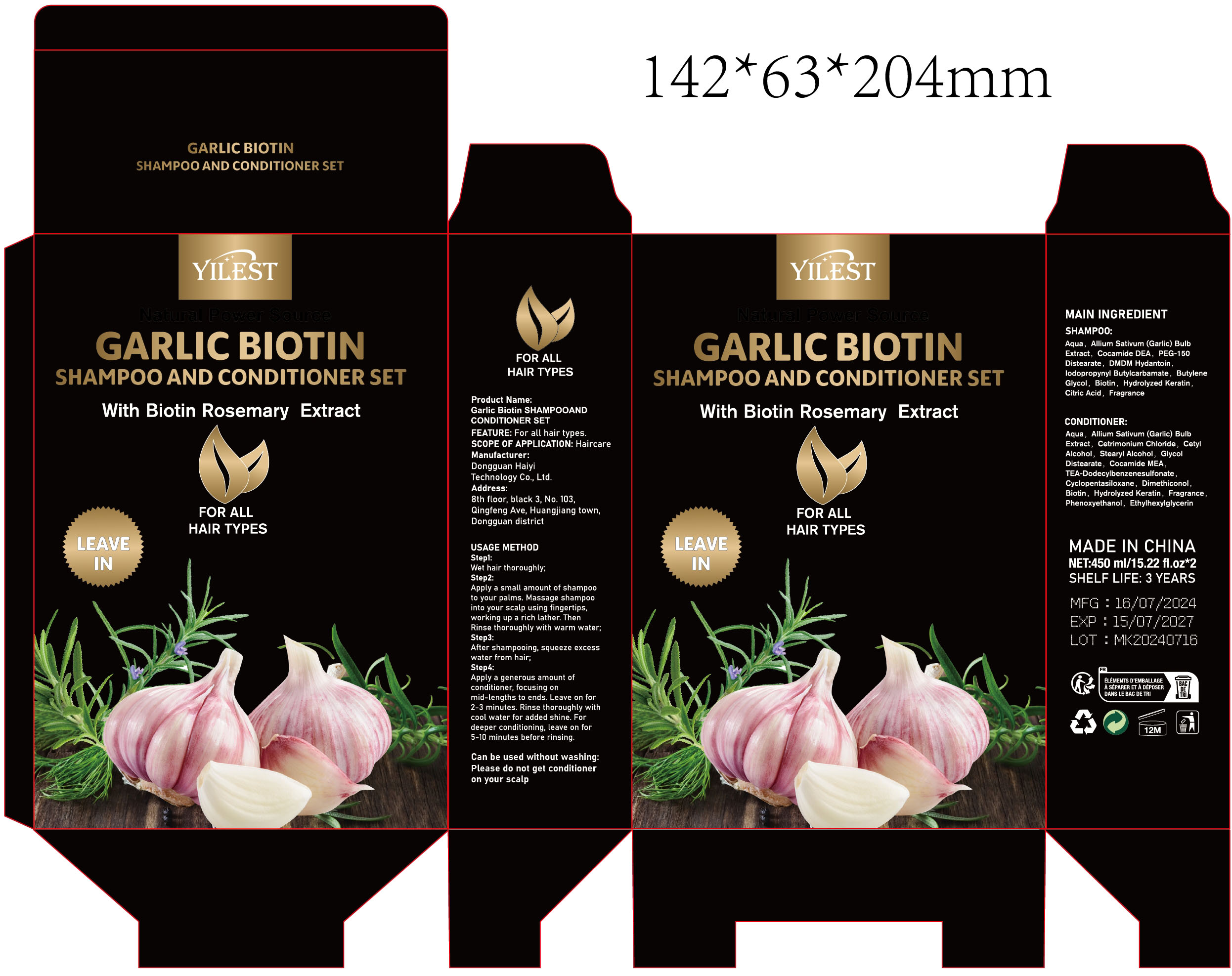 DRUG LABEL: Garlic Biotin
NDC: 84732-069 | Form: SHAMPOO
Manufacturer: Dongguan Haiyi Technology Co.,Ltd.
Category: otc | Type: HUMAN OTC DRUG LABEL
Date: 20241028

ACTIVE INGREDIENTS: ALLIUM SATIVUM (GARLIC) BULB EXTRACT 1 mg/200 mL
INACTIVE INGREDIENTS: BIOTIN; IODOPROPYNYL BUTYLCARBAMATE; WATER; GLYCOL DISTEARATE; CETYL ALCOHOL; CETRIMONIUM CHLORIDE; COCAMIDE DEA; DMDM HYDANTOIN; PEG-150 DISTEARATE; CITRIC ACID; BUTYLENE GLYCOL; COCODIMONIUM HYDROXYPROPYL HYDROLYZED KERATIN (1000 MW); STEARYL ALCOHOL; FRAGRANCE 13576

Active ingredient

Allium Sativum(Garlic) Bulb Extract

Inactive ingredient

SHAMPOO:

Aqua, Cocamide DEA, PEG-150 Distearate, DMDM Hydantoin,lodopropynyl Butylcarbamate, ButyleneGlycol, Biotin, Hydrolyzed Keratin,Citric Acid, Fragrance
CONDITIONER:
Aqua, Cetrimonium Chloride, Cety!Alcohol,Stearyl Alcohol,GlycolDistearate,Cocamide MEATEA-Dodecylbenzenesulfonate，Cyclopentasiloxane, DimethiconolBiotin, Hydrolyzed Keratin, FragrancePhenoxyethanol,Ethylhexylglycerin

Purpose section

Makes hair smoother

Warning

1).For external use only, avoid directcontact with eyes, lf you feel any
discomfort, stop using itand wash it with plenty of water. In severe cases,
pleaseseek medical attention in time.
2). Not allowed to be used ondamaged skin,

stop use

This product may cause allergic reactions in asmall number of people.
lf youexperience any discomfort,please stop using it immediately.

not use

Not suitable for use by children, pregnantor breast feeding people.

OUT OF CHILDREN

KEEP THE PRODUCT OUT OF REACH OF CHILDREN to

HOW TO USE

Step1:Wet hair thoroughly;

Step2:Apply a small amount of shampooto your palms. Massage shampoointo your scalp using fingertips,working up a rich lather. ThenRinse thoroughly with warm water;

Step3:After shampooing, squeeze excesswater from hair;

Step4:Apply a generous amount ofconditioner, focusing onmid-lengths to ends. Leave on for2-3 minutes. Rinse thoroughly withcool water for added shine. Fordeeper conditioning, leave on for5-10 minutes before rinsing.

DOSAGE

1. Normal to oily hair: Every 1-2 days, as it helps manage oil buildup.
2. Dry or curly hair: Every 3-7 days to prevent stripping natural oils.
3. Fine or thin hair: Every other day to maintain volume and avoid weighing down the hair.
4. Coarse, textured, or color-treated hair: Every 3-5 days, as these hair types often retain moisture better and are prone to dryness with frequent washing.